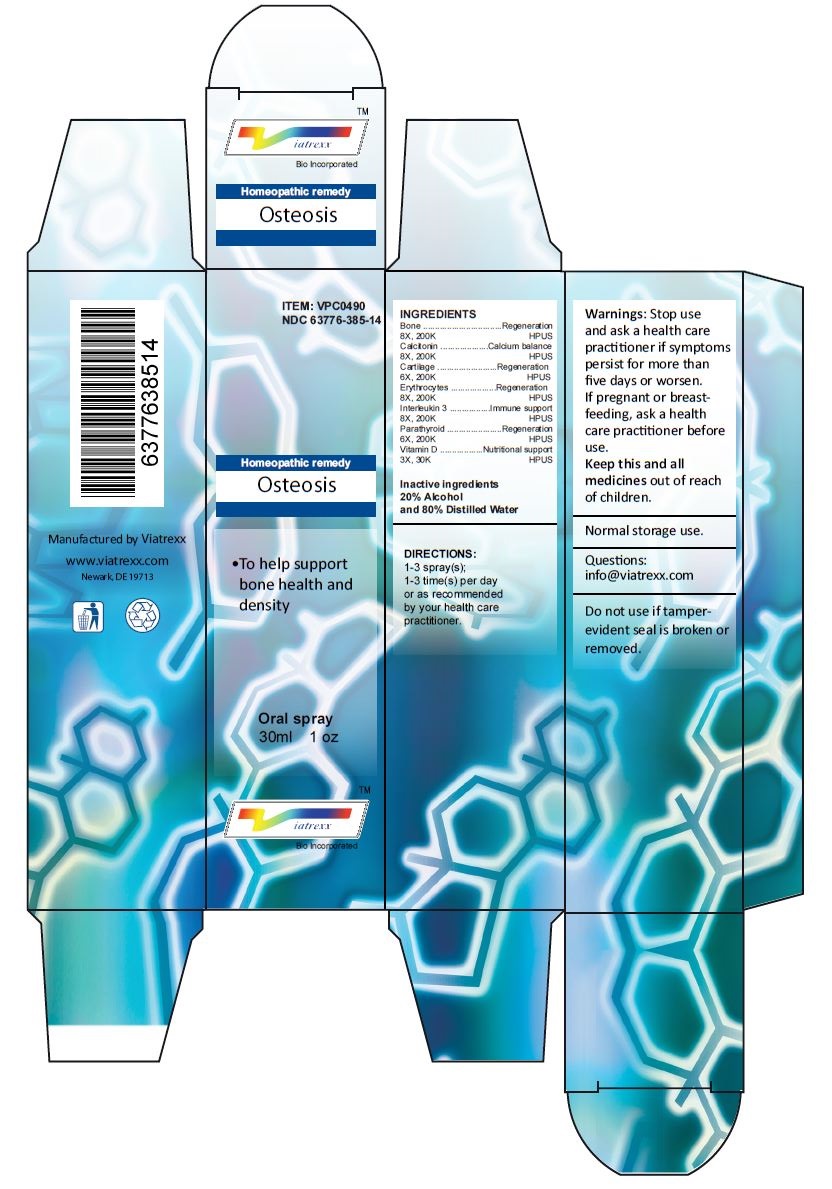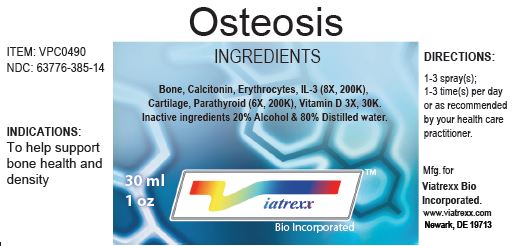 DRUG LABEL: Osteosis
NDC: 63776-385 | Form: SPRAY
Manufacturer: VIATREXX BIO INCORPORATED
Category: homeopathic | Type: HUMAN OTC DRUG LABEL
Date: 20221130

ACTIVE INGREDIENTS: BOS TAURUS BONE 200 [kp_C]/1 mL; SUS SCROFA BONE 200 [kp_C]/1 mL; CALCITONIN 200 [kp_C]/1 mL; BOS TAURUS CARTILAGE 200 [kp_C]/1 mL; SUS SCROFA CARTILAGE 200 [kp_C]/1 mL; BOS TAURUS RED BLOOD CELL 200 [kp_C]/1 mL; SUS SCROFA RED BLOOD CELL 200 [kp_C]/1 mL; INTERLEUKIN-3 200 [kp_C]/1 mL; BOS TAURUS PARATHYROID GLAND 200 [kp_C]/1 mL; SUS SCROFA PARATHYROID GLAND 200 [kp_C]/1 mL; VITAMIN D 30 [kp_C]/1 mL
INACTIVE INGREDIENTS: ALCOHOL; WATER

Osteosis

Active Ingredients

Bone (8X, 200K), Calcitonin (8X, 200K), Cartilage (6X, 200K), Erythrocytes (8X, 200K), Interleukin 3 (8X, 200K), Parathyroid (6X, 200K), Vitamin D (3X, 30K)

Purpose:

Bone | Regeneration
Calcitonin | Calcium balance
Cartilage | Regeneration
Erythrocytes | Regeneration
Interleukin 3 | Immune support
Parathyroid | Regeneration
Vitamin D | Nutritional support

Uses

To help support bone health and density

Warnings

Stop use and ask a health care practitioner if symptoms persist for more than five days or worsen. If pregnant or breastfeeding, ask a health care practitioner before use.

Dosage

1-3 spray(s); 1-3 time(s) per day or as recommended by your health care practitioner.

KEEP OUT OF REACH OF CHILDREN

Keep this and all medicines out of reach of children.

Inactive Ingredients

20% Alcohol and 80% Water

Other Information

Normal storage use.
Do not use if tamper-evident seal is broken or removed.

Questions

info@viatrexx.com

Principal Display Panel

ITEM: VPC0490
NDC 63776-385-14
Homeopathic remedy
Osteosis
• To help support bone health and density
Oral spray
30ml 1 oz
Viatrexx™ Bio Incorporated
Manufactured by Viatrexx
www.viatrexx.com
Newark, DE 19713

Osteosis
30 ml
1 oz
Viatrexx™ Bio Incorporated
ITEM: VPC0490
NDC: 63776-385-14
INDICATIONS:
To help support bone health and density
DIRECTIONS:
1-3 spray(s); 1-3 time(s) per day or as recommended by your health care practitioner.
Mfg. for
Viatrexx Bio Incorporated.
www.viatrexx.com
Newark, DE 19713